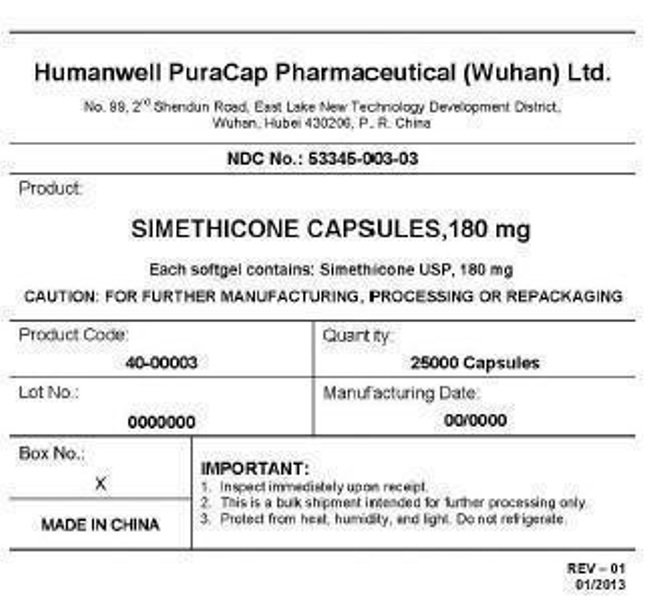 DRUG LABEL: Gas Relief Ultra Strength
NDC: 53345-003 | Form: CAPSULE, LIQUID FILLED
Manufacturer: Humanwell PuraCap Pharmaceutical (Wuhan), Ltd.
Category: otc | Type: HUMAN OTC DRUG LABEL
Date: 20241120

ACTIVE INGREDIENTS: DIMETHICONE 410 180 mg/1 1
INACTIVE INGREDIENTS: SILICON DIOXIDE; FD&C YELLOW NO. 6; GELATIN; GLYCERIN; WATER

SIMETHICONE 180 mg capsule, liquid filled

Active ingredient (in each capsule)

Simethicone 180 mg

Purpose

Antiflatulent

Usesfor relief of:

- bloating
- pressure
- fullness
- stuffed feeling commonly referred to as gas

Warnings

Stop use and ask a doctorif condition persists.

PREGNANCY OR BREAST FEEDING

If pregnant or breast-feeding, ask a health care professional before use.

Keep out of reach of children. In case of overdose, get medical help or contact a Poison Control Center right away.

Directions

- swallow 1 or 2 softgels as needed after meals
- do not exceed 2 softgels per day unless directed by doctor

Other information

- store at controlled room temperature 15°-30°C (59°-86°F)
- protect from heat and moisture
- do not use if imprinted safety seal under cap is broken or missing

Inactive ingredients

FD&C yellow#6, gelatin, glycerin, purified water, sorbitol special and white edible ink.

Manufactured by:
Humanwell PuraCap Pharmaceutical (Wuhan) Ltd.
Wuhan, Hubei
430206, China

PRINCIPAL DISPLAY PANEL - Shipping Label

SIMETHICONE CAPSULES,180 mg

Quantity : 25000 Capsules
NDC. No : 53345-003-03

IMPORTANT:

Inspect immediate upon receipt.
This is a bulk shipment intended for further processing only.
Protect from heat, humidity, and light. Do not refrigerate.

CAUTION : "FOR FURTHER MANUFACTURING, PROCESSING OR REPACKING"